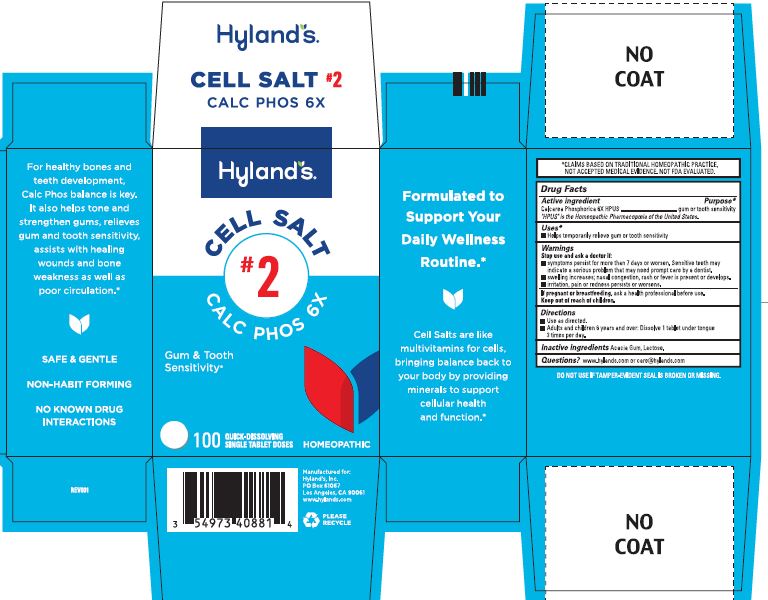 DRUG LABEL: CALC PHOS 6X
NDC: 54973-4088 | Form: TABLET, SOLUBLE
Manufacturer: Hyland's Inc.
Category: homeopathic | Type: HUMAN OTC DRUG LABEL
Date: 20241107

ACTIVE INGREDIENTS: TRIBASIC CALCIUM PHOSPHATE 6 [hp_X]/1 1
INACTIVE INGREDIENTS: ACACIA; LACTOSE MONOHYDRATE

Cell Salt #2 Calc Phos 6X

PURPOSE

Gum or Tooth Sensitivity

Teething Pain

Drug Facts

Active ingredient | Purpose
Calcarea Phosphorica 6X HPUS | gum or tooth sensitivity

"HPUS" is the Homeopathic Pharmacopoeia of the United States.

Uses

■ Helps temporarily relieve gum or tooth sensitivity

Warnings

Stop use and ask a doctor if

■ symptoms persist for more than 7 days or worsen. Sensitive teeth may indicate a serious problem that may need prompt care by a dentist.
■ swelling increases; nasal congestion, rash or fever is present or develops.
■ irritation, pain or redness persists or worsens.

If pregnant or breastfeeding

Ask a health professional before use.

Directions

■ Use as directed.
■ Adults and children 6 years and over: Dissolve 1 tablet under tongue 3 times per day.

Inactive ingredients

Acacia Gum, Lactose.

Questions?

www.hylands.com or care@hylands.com

Indications and Usage (Uses)

update to (add bullet):

Helps temporarily relieve gum or tooth sensitivity

Principal Display Panel

Hyland's

CELL SALT

#2

CALC PHOS 6X

Gum & Tooth

Sensitivity*

100

QUICK-DISSOLVING

SINGLE TABLET DOSES

HOMEOPATHIC